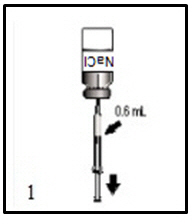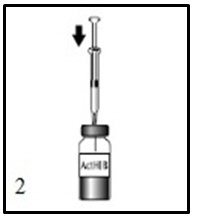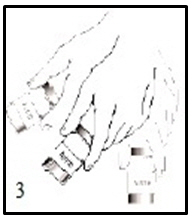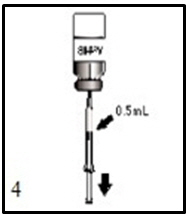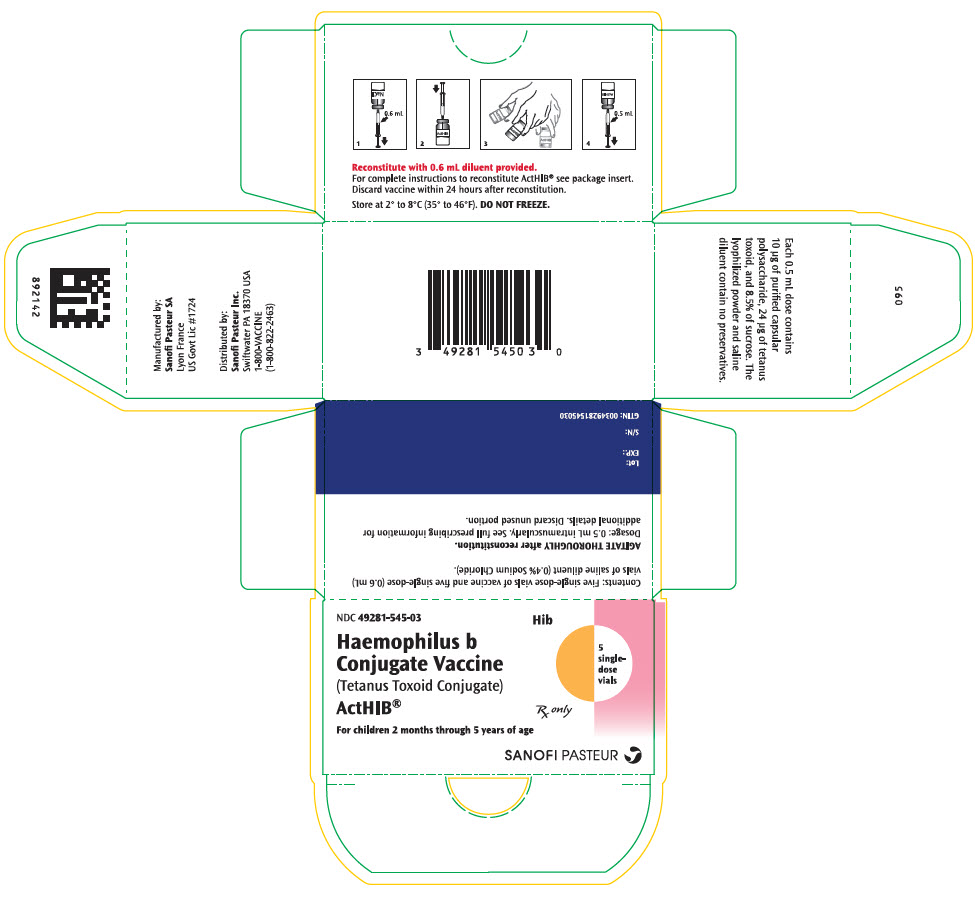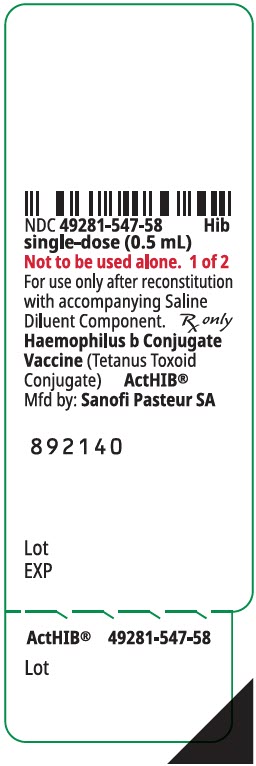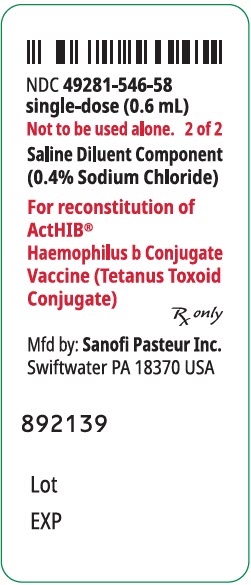 DRUG LABEL: ActHIB
NDC: 49281-545 | Form: KIT | Route: INTRAMUSCULAR
Manufacturer: Sanofi Vaccines US Inc.
Category: other | Type: VACCINE LABEL
Date: 20260129

ACTIVE INGREDIENTS: HAEMOPHILUS INFLUENZAE TYPE B STRAIN 1482 CAPSULAR POLYSACCHARIDE TETANUS TOXOID CONJUGATE ANTIGEN 10 ug/0.5 mL
INACTIVE INGREDIENTS: FORMALDEHYDE; HYDROCHLORIC ACID; SODIUM CHLORIDE 4 mg/1 mL; WATER

HIGHLIGHTS OF PRESCRIBING INFORMATION

These highlights do not include all the information needed to use ActHIB® safely and effectively. See full prescribing information for ActHIB.
ActHIB [Haemophilus b Conjugate Vaccine (Tetanus Toxoid Conjugate)] Solution for Intramuscular Injection
Initial U.S. Approval: 1993

1 INDICATIONS AND USAGE

- ActHIB is a vaccine indicated for the prevention of invasive disease caused by Haemophilus influenzae type b. ActHIB vaccine is approved for use as a four dose series in infants and children 2 months through 5 years of age (1)

2 DOSAGE AND ADMINISTRATION

For intramuscular administration only

Four-dose series (0.5 mL each) by intramuscular injection:

- A three-dose primary series administered at 2, 4, and 6 months of age. (2.1)
- A single booster dose administered at 15-18 months of age. (2.1)

3 DOSAGE FORMS AND STRENGTHS

Solution for injection: lyophilized powder to be reconstituted in supplied 0.4% Sodium Chloride diluent. A single dose, after reconstitution is 0.5 mL (3)

4 CONTRAINDICATIONS

Severe allergic reaction (e.g., anaphylaxis) after a previous dose of any Haemophilus influenzae type b or tetanus toxoid-containing vaccine or any component of ActHIB vaccine. (4)

5 WARNINGS AND PRECAUTIONS

- If Guillain-Barré syndrome occurred within 6 weeks of receipt of a prior vaccine containing tetanus toxoid, the potential benefits and risks of giving ActHIB vaccine must be evaluated. (5.2)

6 ADVERSE REACTIONS

Following administration of ActHIB vaccine in children 2-20 months of age, rates of adverse reactions varied by dose number and age of recipients:

- The most frequent systemic reactions after any dose for children 2 months to 16 months of age were fussiness/irritability (75%), inconsolable crying (58%) and decreased activity/lethargy (51%). (6.1)
- In children 15-20 months of age tenderness (20%) was the most common local reaction following a single dose. (6.1)

To report SUSPECTED ADVERSE REACTIONS, contact Pharmacovigilance Department, Sanofi Pasteur Inc., Discovery Drive, Swiftwater, PA 18370 at 1-800-822-2463 (1-800-VACCINE) or VAERS at 1-800-822-7967 or http://vaers.hhs.gov.

FULL PRESCRIBING INFORMATION

1 INDICATIONS AND USAGE

ActHIB® is a vaccine indicated for the prevention of invasive disease caused by Haemophilus influenzae (H. influenzae) type b. ActHIB is approved for use in children 2 months through 5 years of age.

2 DOSAGE AND ADMINISTRATION

For intramuscular use only

2.1 Immunization Series

ActHIB vaccine is administered as a four-dose series (0.5 mL per dose) as:

- A primary three-dose series of a single dose at 2, 4, and 6 months of age.
- A single booster dose at 15 through 18 months of age.

2.2 Reconstitution

ActHIB vaccine is a solution for injection supplied as single-dose vials of lyophilized vaccine (vial 1 of 2) to be reconstituted only with the accompanying saline diluent (0.4% Sodium Chloride) (vial 2 of 2). To reconstitute ActHIB vaccine, withdraw 0.6 mL of saline diluent and inject into the vial of lyophilized ActHIB vaccine. Agitate the vial to ensure complete reconstitution. The reconstituted ActHIB vaccine will appear clear and colorless. Withdraw a 0.5-mL dose of the reconstituted vaccine and inject intramuscularly. After reconstitution, if ActHIB vaccine is not administered promptly store at 2° to 8°C (35° to 46°F) and administer within 24 hours. Stored vaccine should be re-agitated prior to injection. Refer to Figures 1, 2, 3, and 4.

Instructions for Reconstitution of ActHIB Vaccine with Saline Diluent (0.4% Sodium Chloride)

Figure 1.
Disinfect the diluent vial stopper, inject the needle and withdraw 0.6 mL of 0.4% Sodium Chloride diluent as indicated.

Figure 2.
Cleanse the ActHIB vaccine stopper, insert the syringe needle into the vial, and inject the total volume of diluent.

Figure 3.
Agitate vial thoroughly.

Figure 4.
After reconstitution, withdraw 0.5 mL of reconstituted vaccine and administer intramuscularly.

2.3 Administration

Parenteral drug products should be inspected visually for particulate matter and/or discoloration prior to administration, whenever solution and container permit. If either of these conditions exist, the vaccine should not be administered.

ActHIB vaccine is administered as a single dose (0.5 mL) by intramuscular injection into the anterolateral aspect of the thigh or deltoid. Discard unused portion.

Do not administer this product intravenously, intradermally, or subcutaneously.

ActHIB vaccine should not be mixed in the same syringe with other parenteral products.

3 DOSAGE FORMS AND STRENGTHS

ActHIB vaccine is a solution for injection supplied as a single-dose vial of lyophilized powder to be reconstituted with the supplied 0.4% Sodium Chloride diluent. A single dose, after reconstitution is 0.5 mL.

4 CONTRAINDICATIONS

4.1 Hypersensitivity

Severe allergic reaction (e.g., anaphylaxis) after a previous dose of any H. influenzae type b or tetanus toxoid-containing vaccine or any component of the vaccine is a contraindication to administration of ActHIB vaccine [see DESCRIPTION (11)].

5 WARNINGS AND PRECAUTIONS

5.1 Management of Acute Allergic Reactions

Epinephrine and other appropriate agents must be available should an acute anaphylactic reaction occur.

5.2 Guillain-Barré Syndrome

If Guillain-Barré syndrome has occurred within 6 weeks of receipt of a prior vaccine containing tetanus toxoid, the decision to give any tetanus toxoid-containing vaccine, including ActHIB vaccine, should be based on careful consideration of the potential benefits and possible risks.

5.3 Altered Immunocompetence

In immunosuppressed persons, including those receiving immunosuppressive therapy, the expected antibody responses may not be obtained.

5.4 Limitations of Vaccine Effectiveness

Vaccination with ActHIB vaccine may not protect 100% of individuals.

5.5 Tetanus Immunization

Immunization with ActHIB vaccine does not substitute for routine tetanus immunization.

5.6 Interference with Laboratory Tests

Urine antigen detection may not have a diagnostic value in suspected disease due to H. influenzae type b within 1 to 2 weeks after receipt of a H. influenzae type b-containing vaccine, including ActHIB [see DRUG INTERACTIONS (7.3)].

5.7 Syncope

Syncope (fainting) has been reported following vaccination with ActHIB. Procedures should be in place to avoid injury from fainting.

6 ADVERSE REACTIONS

6.1 Clinical Trials Experience

Because clinical trials are conducted under widely varying conditions, adverse reaction rates observed in the clinical trials of a vaccine cannot be directly compared to rates in the clinical trials of another vaccine and may not reflect the rates observed in practice.

More than 7,000 infants and young children (≤2 years of age) have received at least one dose of ActHIB vaccine during US clinical trials. Of these, 1,064 subjects 12 to 24 months of age who received ActHIB vaccine alone reported no serious or life threatening adverse reactions.(1) (2)

Adverse reactions associated with ActHIB vaccine generally subsided after 24 hours and did not persist beyond 48 hours after immunization.

In a US trial, the safety of ActHIB vaccine was evaluated in 110 children 15 to 20 months of age. All children received three doses of Haemophilus influenzae type b conjugate vaccine (ActHIB vaccine or a previously licensed Haemophilus b conjugate vaccine) at approximately 2, 4, and 6 months of age. The incidence of selected solicited injection site and systemic adverse reactions which occurred within 48 hours following the dose of ActHIB vaccine is shown in Table 1.

Table 1: Local and Systemic Reactions at 6, 24, and 48 Hours Following Immunization with ActHIB Vaccine in Children 15 to 20 months old (2)
Adverse Event | 6 Hrs. Post-dose | 24 Hrs. Post-dose | 48 Hrs. Post-dose
Local (%) | N=110 | N=110 | N=110
Tenderness | 20.0 | 8.2 | 0.9
Erythema (>1") | 0.0 | 0.9 | 0.0
Induration [Induration is defined as hardness with or without swelling.] | 5.5 | 3.6 | 0.9
Swelling | 3.6 | 1.8 | 0.0
Systemic (%) | N=103-110 | N=105-110 | N=104-110
Fever (>102.2°F) (>39.0°C) | 0 | 1.0 | 1.9
Irritability | 27.3 | 20.9 | 12.7
Drowsiness | 36.4 | 17.3 | 12.7
Anorexia | 12.7 | 10.0 | 6.4
Vomiting | 0.9 | 0.9 | 0.9
Persistent cry | 0 | 0 | 0
Unusual cry | 0 | 0 | 0

In a US clinical trial (P3T06), 1,454 children were enrolled and received one dose of ActHIB vaccine at 2 months of age and subsequent doses administered at 4 and 6 months of age (concomitantly with DAPTACEL [a US-licensed diphtheria, tetanus and pertussis vaccine], IPOL [a US-licensed inactivated poliovirus vaccine] and PCV7 [Pneumococcal conjugate vaccine, 7-valent]) vaccines at 2, 4, and 6 months of age and hepatitis B vaccine at 2 and 6 months of age). At 15-16 months of age, 418 children received a 4th dose of ActHIB and DAPTACEL vaccines. The most frequent systemic reactions following any dose (>50% of participants) were decreased activity/lethargy, fussiness/irritability, and inconsolable crying.

Table 2: Number (Percentage) of Children with Selected Solicited Systemic Adverse Reactions by Severity Occurring within 0-3 days After Vaccination in Study P3T06
Systemic Reactions | DAPTACEL + IPOL + ActHIB Vaccines |  |  | DAPTACEL + ActHIB Vaccines
Systemic Reactions | Dose 1 N=1,390-1,406 % | Dose 2 N=1,346-1,360 % | Dose 3 N=1,301-1,312 % | Dose 4 N=379-381 %
Fever [Fever is based upon actual temperatures recorded with no adjustments to the measurement route.] [Following Doses 1-3 combined, the proportion of temperature measurements that were taken by axillary, rectal or other routes, or not recorded were 44.8%, 54.0%, 1.0%, and 0.1%, respectively. Following Dose 4, the proportion of temperature measurements that were taken by axillary, rectal or other routes, or not recorded were 61.1%, 36.6%, 1.7%, and 0.5%, respectively.]
≥38.0°C | 9.3 | 16.1 | 15.8 | 8.7
>38.5°C | 1.6 | 4.3 | 5.1 | 3.2
>39.5°C | 0.1 | 0.4 | 0.3 | 0.8
Decreased Activity/Lethargy [Moderate: interferes with or limits usual daily activity; Severe: disabling, not interested in usual daily activity.]
Any | 51.1 | 37.4 | 33.2 | 24.1
Moderate or Severe | 24.3 | 15.8 | 12.7 | 9.2
Severe | 1.2 | 1.4 | 0.6 | 0.3
Inconsolable Crying
Any | 58.5 | 51.4 | 47.9 | 36.2
≥1 hour | 16.4 | 16.0 | 12.2 | 10.5
>3 hours | 2.2 | 3.4 | 1.4 | 1.8
Fussiness/Irritability
Any | 75.8 | 70.7 | 67.1 | 53.8
≥1 hour | 33.3 | 30.5 | 26.2 | 19.4
>3 hours | 5.6 | 5.5 | 4.3 | 4.5
Note. - Ages of study participants ranged from 1.3 to 19.5 months.

In Study P3T06, within 30 days following any of Doses 1-3 of DAPTACEL + IPOL + ActHIB vaccines, 50 of 1,455 (3.4%) participants experienced a serious adverse event (SAE). One SAE of seizure with apnea occurring on the day of vaccination with the first dose of the three vaccines was determined by the investigators as possibly related. Within 30 days following Dose 4, four of 418 (1.0%) participants who received DAPTACEL + ActHIB vaccines experienced a serious adverse event. None was assessed by the investigators as related to the study of vaccines.

6.2 Postmarketing Experience

The following events have been spontaneously reported during the post-approval use of ActHIB vaccine. Because these events are reported voluntarily from a population of uncertain size, it is not always possible to reliably estimate their frequency or establish a causal relationship to vaccine exposure.

- Immune system disorders:
  Anaphylaxis, other allergic/hypersensitivity reactions (including urticaria, angioedema)
- Nervous system disorders:
  Convulsions, syncope
- General disorders and administration site conditions:
  Extensive limb swelling, peripheral edema, pruritus, rash (including generalized rash)

7 DRUG INTERACTIONS

7.1 Concomitant Administration with Other Vaccines

In clinical trials, ActHIB vaccine was administered, at separate sites, concomitantly with one or more of the following vaccines: DTaP; Measles, Mumps and Rubella vaccine (MMR); Hepatitis B vaccine; and Inactivated Poliovirus Vaccine (IPV). No impairment of the antibody response to the individual antigens was demonstrated when ActHIB vaccine was given at the same time but separate sites with these vaccines.(2)

7.2 Immunosuppressive Treatments

Immunosuppressive therapies, including irradiation, antimetabolites, alkylating agents, cytotoxic drugs, and corticosteroids (used in greater than physiologic doses) may reduce the immune response to ActHIB vaccine [see WARNINGS AND PRECAUTIONS (5.3)].

7.3 Interference with Laboratory Tests

Haemophilus b capsular polysaccharide derived from Haemophilus b Conjugate Vaccines has been detected in the urine of some vaccinees. Urine antigen detection may not have a diagnostic value in suspected disease due to H. influenzae type b within 1 to 2 weeks after receipt of a H. influenzae type b-containing vaccine, including ActHIB [see WARNINGS AND PRECAUTIONS (5.6)].(3)

8 USE IN SPECIFIC POPULATIONS

8.1 Pregnancy

ActHIB is not approved for use in individuals 6 years of age and older. No human or animal data are available to assess vaccine-associated risks in pregnancy.

8.2 Lactation

ActHIB is not approved for use in individuals 6 years of age and older. Human or animal data are not available to assess the impact of ActHIB on milk production, its presence in breast milk, or its effects on the breastfed infant.

8.4 Pediatric Use

Safety and effectiveness of ActHIB have not been established in infants below the age of 6 weeks and children and adolescents 6 years of age and older [see DOSAGE AND ADMINISTRATION (2.1)].

11 DESCRIPTION

ActHIB vaccine is a sterile, lyophilized powder to be reconstituted with saline diluent (0.4% Sodium Chloride) for intramuscular administration only. The vaccine consists of the Haemophilus influenzae type b capsular polysaccharide (polyribosyl-ribitol-phosphate, PRP), a high-molecular-weight polymer prepared from the H. influenzae type b strain 1482 grown in a semi-synthetic medium, covalently bound to tetanus toxoid. (4) The lyophilized ActHIB vaccine powder and saline diluent contain no preservative. The tetanus toxoid is prepared by extraction, ammonium sulfate purification, and formalin inactivation of the toxin from cultures of Clostridium tetani (Harvard strain) grown in a modified Mueller and Miller medium. (5) The culture medium contains milk-derived raw materials (casein derivatives). Further manufacturing process steps reduce residual formaldehyde to levels below 0.5 micrograms (mcg) per dose by calculation. The toxoid is filter sterilized prior to the conjugation process. In the final formulated vaccine, pH is adjusted using hydrochloric acid. Potency of ActHIB vaccine is specified on each lot by limits on the content of PRP polysaccharide and protein in each dose and the proportion of polysaccharide and protein in the vaccine that is characterized as high molecular weight conjugate.

When ActHIB is reconstituted with saline diluent (0.4% Sodium Chloride), each 0.5-mL dose is formulated to contain 10 mcg of purified capsular polysaccharide conjugated to 24 mcg of inactivated tetanus toxoid and 8.5% of sucrose.

The vial stoppers for ActHIB vaccine and diluent are not made with natural rubber latex.

12 CLINICAL PHARMACOLOGY

12.1 Mechanism of Action

Haemophilus influenzae is a gram-negative coccobacillus. Most strains of H. influenzae that cause invasive disease (e.g., sepsis and meningitis) are H. influenzae type b.

The response to ActHIB vaccine is typical of a T-dependent immune response to antigens. The prominent isotype of anti-capsular PRP antibody induced by ActHIB vaccine is IgG. (6) A booster response for IgG has been demonstrated in children 12 months of age or older who previously received two or three doses of ActHIB vaccine. Bactericidal activity against H. influenzae type b was demonstrated in serum after immunization and correlated with the anti-PRP antibody response induced by ActHIB vaccine. (1)

Antibody titers to H. influenzae capsular polysaccharide (anti-PRP) of >1.0 mcg/mL following vaccination with unconjugated PRP vaccine correlated with long-term protection against invasive H. influenzae type b disease in children older than 24 months of age. (7) Although the relevance of this threshold to clinical protection after immunization with conjugate vaccines is not known, particularly in light of the induced, immunologic memory, this level continues to be considered as indicative of long-term protection. (8) In clinical studies, ActHIB vaccine induced, on average, anti-PRP levels ≥1.0 mcg/mL in 90% of infants after the primary series (2, 4, and 6 months) and in more than 98% of infants following a booster dose given at 15 to 19 months of age. (1)

13 NON-CLINICAL TOXICOLOGY

13.1 Carcinogenesis, Mutagenesis, Impairment of Fertility

ActHIB vaccine has not been evaluated for its carcinogenic or mutagenic potential or impairment of male fertility.

14 CLINICAL STUDIES

14.1 Immunogenicity of ActHIB Vaccine in Children 2, 4 and 6 Months of Age

Two clinical trials supported by the National Institutes of Health (NIH) have compared the anti-PRP antibody responses to three Haemophilus influenzae type b conjugate vaccines in racially mixed populations of children. These studies were done in Tennessee (9) (Table 3) and in Minnesota, Missouri, and Texas (10) (Table 4) in infants immunized with ActHIB vaccine and other Haemophilus influenzae type b conjugate vaccines at 2, 4, and 6 months of age. All Haemophilus influenzae type b conjugate vaccines were administered concomitantly with OPV and whole-cell DTP vaccines at separate sites. Neither OPV nor whole-cell DTP vaccines are licensed or distributed in the US currently.

Table 3: Anti-PRP Antibody Responses Following a Two or Three Dose Series of a Haemophilus influenzae type b Vaccine at 2, 4, and 6 Months of Age – Tennessee (9)
Vaccine | N [N = Number of children] | Geometric Mean Concentration (GMC) (mcg/mL) |  |  | Post Third Immunization % ≥1.0 mcg/mL
Vaccine | N [N = Number of children] | Pre-Immunization at 2 months | Post Second Immunization at 6 months | Post Third Immunization at 7 months | Post Third Immunization % ≥1.0 mcg/mL
PRP-T [Haemophilus influenzae type b Conjugate Vaccine (Tetanus Toxoid Conjugate)] (ActHIB vaccine) | 65 | 0.10 | 0.30 | 3.64 | 83%
PRP-OMP [Haemophilus influenzae type b Conjugate Vaccine (Meningococcal Protein Conjugate)] (PedvaxHIB®) | 64 | 0.11 | 0.84 | N/A | 50% [Seroconversion after the recommended 2-dose primary immunization series is shown]
HbOC [Haemophilus influenzae type b Conjugate Vaccine (Diphtheria CRM197 Protein Conjugate)] (HibTITER®) | 61 | 0.07 | 0.13 | 3.08 | 75%
N/A = Not applicable in this comparison trial although third dose data have been published

Table 4: Anti-PRP Antibody Responses Following a Two or Three Dose Series of a Haemophilus influenzae type b Vaccine at 2, 4, and 6 Months of Age - Minnesota, Missouri, and Texas (10)
Vaccine | N [N = Number of children] | Geometric Mean Concentration (GMC) (mcg/mL) |  |  | Post Third [Sera were obtained after the third dose from 86 and 110 infants, in PRP-T and HbOC vaccine groups, respectively] Immunization % ≥1.0 mcg/mL
Vaccine | N [N = Number of children] | Pre-Immunization at 2 months | Post Second Immunization at 6 months | Post Third Immunization at 7 months | Post Third [Sera were obtained after the third dose from 86 and 110 infants, in PRP-T and HbOC vaccine groups, respectively] Immunization % ≥1.0 mcg/mL
PRP-T [Haemophilus influenzae type b Conjugate Vaccine (Tetanus Toxoid Conjugate)] (ActHIB vaccine) | 142 | 0.25 | 1.25 | 6.37 | 97%
PRP-OMP [Haemophilus influenzae type b Conjugate Vaccine (Meningococcal Protein Conjugate)] (PedvaxHIB) | 149 | 0.18 | 4.00 | N/A | 85% [Seroconversion after the recommended 2-dose primary immunization series is shown]
HbOC [Haemophilus influenzae type b Conjugate Vaccine (Diphtheria CRM197 Protein Conjugate)] (HibTITER) | 167 | 0.17 | 0.45 | 6.31 | 90%
N/A = Not applicable in this comparison trial although third dose data have been published (10)

Native American populations have had high rates of H. influenzae type b disease and have been observed to have low immune responses to Haemophilus influenzae type b conjugate vaccines. In a clinical study enrolling Alaskan Native Americans, following the administration of a three-dose series of ActHIB vaccine at 6 weeks, 4 months, and 6 months of age, 75% of subjects achieved an anti-PRP antibody titer of ≥1.0 mcg/mL at 7 months of age (1 month after the last vaccination). (11)

14.2 Immunogenicity of ActHIB Vaccine in Children 12 to 24 Months of Age

In four separate studies, children 12 to 24 months of age who had not previously received Haemophilus influenzae type b conjugate vaccination were immunized with a single dose of ActHIB vaccine (Table 5). Geometric Mean Concentration (GMC) of anti-PRP antibody responses were 5.12 mcg/mL (90% responding with ≥1.0 mcg/mL) for children 12 to 15 months of age and 4.4 mcg/mL (82% responding with ≥1.0 mcg/mL) for children 17 to 24 months of age. (2)

Table 5: Anti-PRP Antibody Responses in 12- to 24-month-old Children Immunized with a Single Dose of ActHIB
Age Group | N [N = Number of children] | Geometric Mean Concentration (GMC) (mcg/mL) |  | % Subjects With ≥1.0 mcg/mL
Age Group | N [N = Number of children] | Pre-Immunization | Post-Immunization [Post immunization responses measured at approximately 1 month after vaccination] | Pre-Immunization | Post-Immunization
12 to 15 months | 256 | 0.06 | 5.12 | 1.6 | 90.2
17 to 24 months | 81 | 0.10 | 4.40 | 3.7 | 81.5

ActHIB vaccine has been found to be immunogenic in children with sickle cell anemia, a condition that may cause increased susceptibility to Haemophilus influenzae type b disease. Following two doses of ActHIB vaccine given at two-month intervals, 89% of these children (mean age 11 months) had anti-PRP antibody titers of ≥1.0 mcg/mL. This is comparable to anti-PRP antibody levels demonstrated in children without sickle-cell anemia of similar age following two doses of ActHIB vaccine. (12)

15 REFERENCES

1 Data on file, Sanofi Winthrop Industrie.
2 Data on file, Sanofi Pasteur Inc.
3 Rothstein EP, et al. Comparison of antigenuria after immunization with three Haemophilus influenzae type b conjugate vaccines. Pediatr Infect Dis J 10:311-314, 1991.
4 Chu CY, et al. Further studies on the immunogenicity of Haemophilus influenzae type b and pneumococcal type 6A polysaccharide-protein conjugate. Infect Immun 40:245-246, 1983.
5 Mueller JH, et al. Production of diphtheria toxin of high potency (100 Lf) on a reproducible medium. J Immunol 40:21-32, 1941.
6 Holmes SJ, et al. Immunogenicity of four Haemophilus influenzae type b conjugate vaccines in 17- to 19-month-old children. J Pediatr 118:364-371, 1991.
7 Peltola H, et al. Prevention of Haemophilus influenzae type b bacteremic infections with the capsular polysaccharide vaccine. N Engl J Med 310:1561-1566, 1984.
8 Recommendations of the Immunization Practices Advisory Committee (ACIP). Haemophilus b conjugate vaccines for prevention of Haemophilus influenzae type b disease among infants and children two months of age and older. MMWR 40:No. RR-1, 1991.
9 Decker MD, et al. Comparative trial in infants of four conjugate Haemophilus influenzae type b vaccines. J Pediatr 120:184-189, 1992.
10 Granoff DM, et al. Differences in the immunogenicity of three Haemophilus influenzae type b conjugate vaccines in infants. J Pediatr 121:187-194, 1992.
11 Bulkow LR, et al. Comparative immunogenicity of four Haemophilus influenzae type b conjugate vaccines in Alaska Native infants. Pediatr Infect Dis J 12:484-92, 1993.
12 Kaplan SL, et al. Immunogenicity of Haemophilus influenzae type b polysaccharide-tetanus protein conjugate vaccine in children with sickle hemoglobinopathy or malignancies, and after systemic Haemophilus influenzae type b infection. J Pediatr 120:367-370, 1992.
13 Vaccine Adverse Event Reporting System United States. MMWR 39:730-733, 1990.
14 CDC. National Childhood Vaccine Injury Act: Requirements for permanent vaccination records and for reporting of selected events after vaccination. MMWR 37:197-200, 1988.
15 National Childhood Vaccine Injury Act of 1986 (Amended 1987).

16 HOW SUPPLIED/STORAGE AND HANDLING

16.1 How Supplied

Single-dose, lyophilized vaccine vial (vial 1 of 2) (NDC 49281-547-58) packaged with single-dose diluent vial (vial 2 of 2) (NDC 49281-546-58). Supplied as package of 5 vials each (NDC 49281-545-03).

The vial stoppers for ActHIB vaccine and diluent are not made with natural rubber latex.

16.2 Storage and Handling

Store lyophilized ActHIB vaccine packaged with saline diluent (0.4% Sodium Chloride) at 2° to 8°C (35° to 46°F). DO NOT FREEZE. Discard unused portion.

17 PATIENT COUNSELING INFORMATION

Vaccine Information Statements are required by the National Childhood Vaccine Injury Act of 1986 to be given prior to immunization to the patient, parent, or guardian.

Inform the patients, parents, or guardians about the potential benefits and risks of the vaccine and importance of completing the immunization series unless a contraindication to further immunization exists. In addition to this, parents and guardians must be informed about the potential for adverse reactions that have been temporarily associated with the administration of ActHIB vaccine or other vaccines containing similar ingredients. Prior to administration of ActHIB vaccine, healthcare providers should ask parents or guardians about the recent health status of the infant or child to be immunized. As part of the child's immunization record, the date, lot number, and manufacturer of the vaccine administered should be recorded. (13) (14) (15) Vaccine recipients and guardians must report any adverse reactions upon administration of the vaccine to their healthcare provider and/or to the Vaccine Adverse Event Reporting System (VAERS).

ActHIB, DAPTACEL and IPOL are registered trademarks of Sanofi Pasteur Inc.
PedvaxHIB is a registered trademark of Merck & Co., Inc.
HibTITER is a registered trademark of Nuron Biotech.

Product information
as of January 2026.

Manufactured by:
Sanofi Winthrop Industrie
Marcy L'Etoile France
US Govt License #1724

Distributed by:
Sanofi Pasteur Inc.
Swiftwater PA 18370 USA

PRINCIPAL DISPLAY PANEL - Kit Carton

NDC 49281-545-03

Hib

Haemophilus b
Conjugate Vaccine
(Tetanus Toxoid Conjugate)
ActHIB®

For children 2 months through 5 years of age

5
single-
dose
vials

Rx only

SANOFI PASTEUR

PRINCIPAL DISPLAY PANEL - 0.5 mL Vial Label

NDC 49281-547-58
Hib
single-dose (0.5 mL)

Not to be used alone. 1 of 2
For use only after reconstitution
with accompanying Saline
Diluent Component.
Rx only

Haemophilus b Conjugate
Vaccine (Tetanus Toxoid
Conjugate)
ActHIB®

Mfd by: Sanofi Pasteur SA

892140

Lot
EXP

PRINCIPAL DISPLAY PANEL - 0.6 mL Vial Label

NDC 49281-546-58
single-dose (0.6 mL)

Not to be used alone. 2 of 2

Saline Diluent Component
(0.4% Sodium Chloride)

For reconstitution of
ActHIB®
Haemophilus b Conjugate
Vaccine (Tetanus Toxoid
Conjugate)

Rx only

Mfd by: Sanofi Pasteur Inc.
Swiftwater PA 18370 USA

892139

Lot

EXP